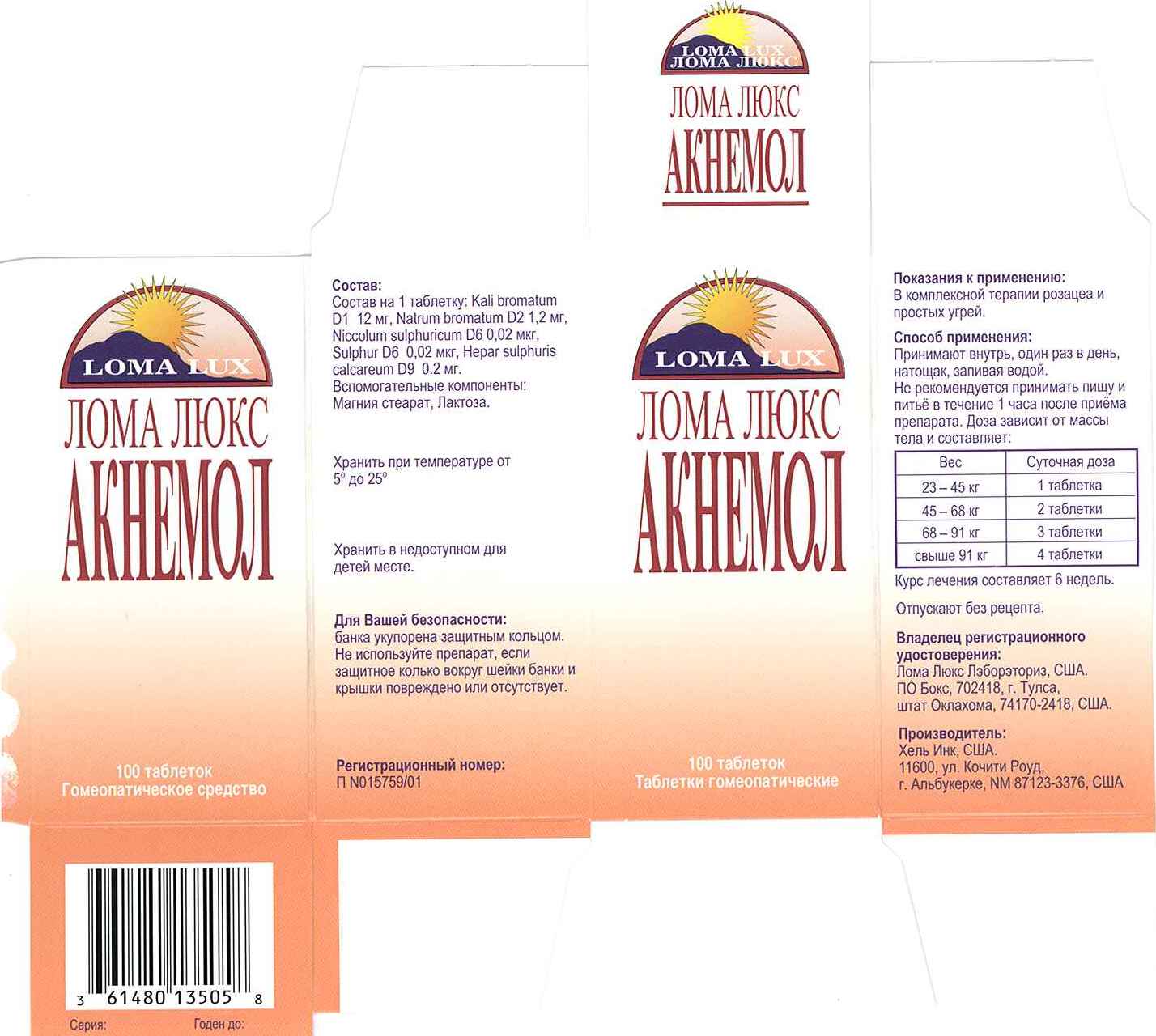 DRUG LABEL: Acne
NDC: 57520-0710 | Form: TABLET
Manufacturer: Apotheca Company
Category: homeopathic | Type: HUMAN OTC DRUG LABEL
Date: 20110715

ACTIVE INGREDIENTS: POTASSIUM BROMIDE 1 [hp_X]/1 1; SODIUM BROMIDE 2 [hp_X]/1 1; NICKEL SULFATE HEXAHYDRATE 6 [hp_X]/1 1; SULFUR 6 [hp_X]/1 1; CALCIUM SULFIDE 9 [hp_X]/1 1
INACTIVE INGREDIENTS: LACTOSE; MAGNESIUM STEARATE

Acne Pill Russia

ACTIVE INGREDIENT

ACTIVE INGREDIENTS: Kali bromatum 1X, Natrum bromatum 2X, Niccolum sulphuricum 6X, Sulphur 6X, Hepar sulphuris calcareum 9X.

PURPOSE

For treatment of the pimples and blemishes of Acne.

WARNINGS

WARNINGS: If symptoms persist or worsen, contact a physician.

If pregnant or nursing, use only under the advice and supervision of a physician.

Keep out of the reach of children.

CAUTION: Use only as directed.

Do not give to children under six years old or use in the presence of kidney disease.

If skin rash appears, or if nervous symptoms persist, recur frequently or are unusual, discontinue use and consult a physician.

SAFETY SEALED for your protection. Do not use if imprinted seal around bottle neck and cap is missing or broken.

DOSAGE AND ADMINISTRATION

DIRECTIONS: Take once per day as indicated on chart below. Continue use as long as it is beneficial to your overall condition.

WEIGHT DAILY DOSAGE

50-100 lbs One tablet

100-150 lbs Two tablets

150-200 lbs Three tablets

Over 200 lbs Four tablets

INACTIVE INGREDIENTS: Lactose, Magnesium stearate.

KEEP OUT OF REACH OF CHILDREN.

INDICATIONS AND USAGE

For treatment of the pimples and blemishes of Acne.

QUESTIONS

Manufactured for and dist by:

LOMA LUX LABORATORIES

P.O. BOX 702418

TULSA, OK 74170-2418

Questions? Call us!

1-866.LOMALUX

More information? Visit our Web Site:

AcnePill.com

PACKAGE LABEL

LOMA LUX

LOMA LUX ACNE PILL

Dermatologist Developed

For treatment of the pimples and blemishes of Acne

TAKE ORALLY

100 TABLETS

HOMEOPATHIC MEDICINE